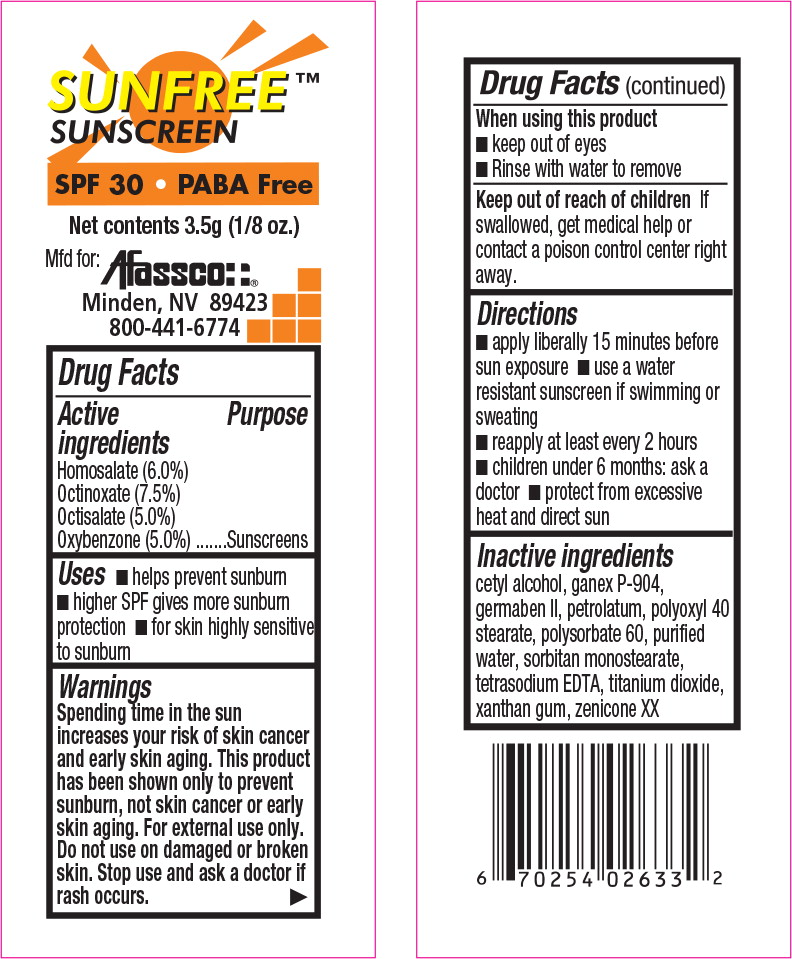 DRUG LABEL: Sunfree Sunscreen
NDC: 51532-6103 | Form: LOTION
Manufacturer: Afassco
Category: otc | Type: HUMAN OTC DRUG LABEL
Date: 20211207

ACTIVE INGREDIENTS: Homosalate 6 mg/1 g; Octinoxate 7.5 mg/1 g; Octisalate 5 mg/1 g; Oxybenzone 5 mg/1 g
INACTIVE INGREDIENTS: cetyl alcohol; ETHYL PYRROLIDONE; propylene glycol; propylparaben; methylparaben; diazolidinyl urea; polyoxyl 40 stearate; polysorbate 60; petrolatum; water; sorbitan monostearate; edetate sodium; titanium dioxide; xanthan gum; Polyethylene Glycol 400; dimethicone; PEG-8 Dimethicone

Drug Facts

Active ingredients

Homosalate (6.0%)

Octinoxate (7.5%)

Octisalate (5.0%)

Oxybenzone (5.0%)

Purpose

Sunscreens

Uses

- helps prevent sunburn
- higher SPF gives more sunburn protection
- for skin highly sensitive to sunburn

Warnings

Spending Time in the sun increases your risk of skin cancer and early skin aging. This product has been shown only to prevent sunburn, not skin cancer or early skin aging. For external use only. Do not use on damaged or broken skin. Stop use and ask a doctor if rash occurs.

When using this product

- keep out of eyes
- Rinse with water to remove

Keep out of reach of children If swallowed, get medical help or contact a poison control center right away.

Directions

- apply liberally 15 minutes before sun exposure
- use a water resistant sunscreen if swimming or sweating
- reapply at least every 2 hours
- children under 6 months: ask a doctor
- protect from excessive heat and direct sun

Inactive ingredients

cetyl alcohol, ganex P-904, germaben II, petrolatum, polyoxyl 40 stearate, polysorbate 60, purified water, sorbitan monostearate, tetrasodium EDTA, titanium dioxide, xanthan gum, zenicone XX

Principal Display Panel - Packet Label

SUNFREE™
SUNSCREEN

SPF 30 PABA Free

Net contents 3.5g (1/8 oz.)

Mfd for:

Afassco::®

Minden, NV 89423

800-441-6774

res